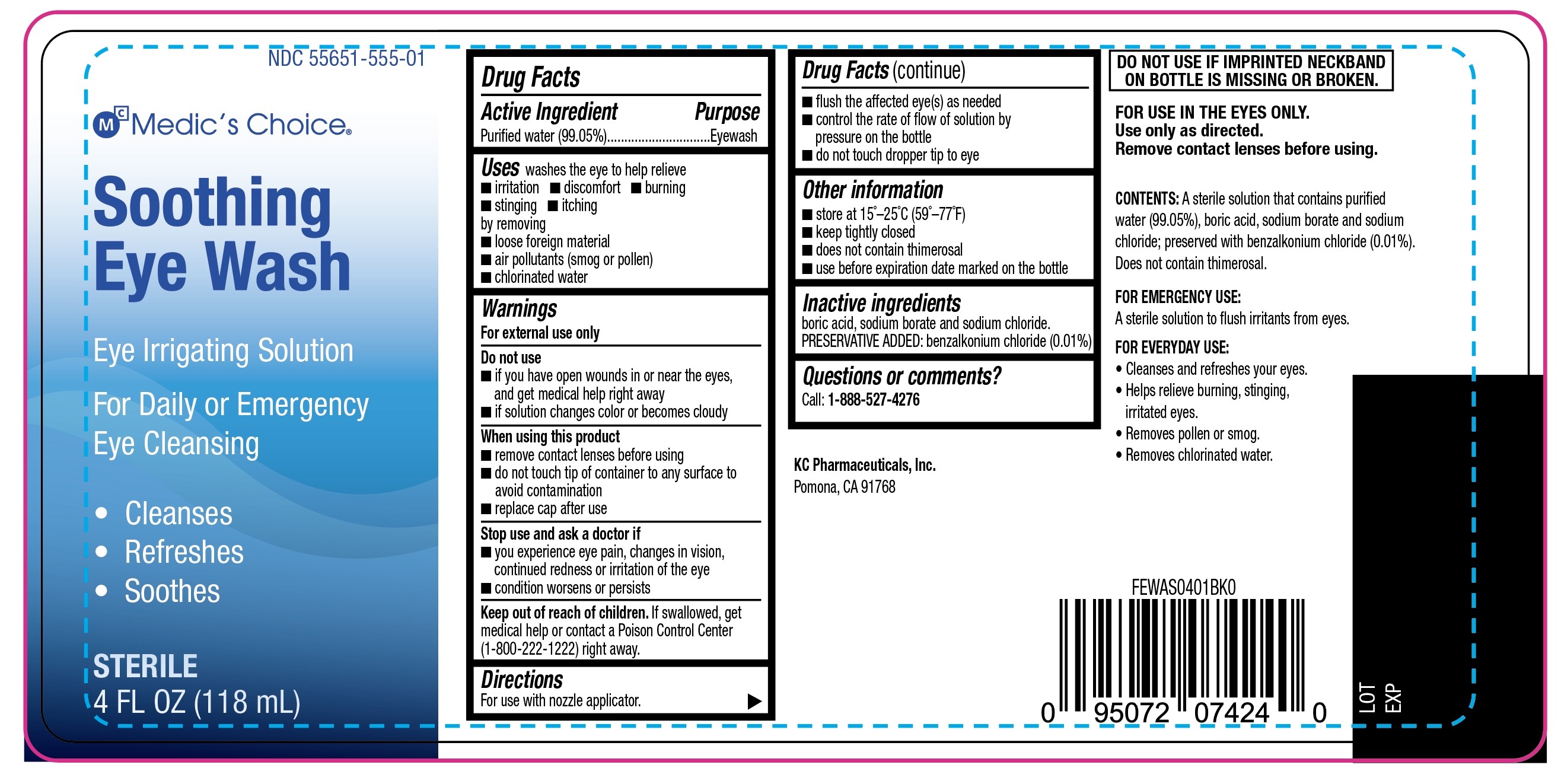 DRUG LABEL: Medics Choice Soothing Eye Wash
NDC: 55651-555 | Form: SOLUTION
Manufacturer: KC Pharmaceuticals, Inc.
Category: otc | Type: HUMAN OTC DRUG LABEL
Date: 20250119

ACTIVE INGREDIENTS: WATER 99.05 g/100 mL
INACTIVE INGREDIENTS: SODIUM CHLORIDE; BENZALKONIUM CHLORIDE; SODIUM BORATE; BORIC ACID

Medic's Choice Soothing Eye Wash 118mL - labeled bottle (PLD)

Active ingredient

Purified water (99.05%)

Purpose

Eyewash

Uses

washes the eye to help relieve

- irritation
- discomfort
- burning
- stinging
- itching

by removing

- loose foreign material
- air pollutants (smog or pollen)
- chlorinated water

Warnings

For external use only

Do not use

- if you have open wounds in or near the eyes, and get medical help right away
- if solution changes color or becomes cloudy

When using this product

- remove contact lenses before using
- do not touch to of container to any surface to avoid contamination
- replace cap after use

Stop use and ask a doctor if

- you experience eye pain, changes in vision, continued redness or irritation of the eye
- condition worsens or persists

Keep out of reach of children.

If swallowed, get medical help or contact a Poison Control Center (1-800-222-1222) right away.

Directions

For use with nozzle applicator.

- flush the affected eye(s) as needed
- control the rate of flow of solution by pressure on the bottle
- do not touch dropper tip to eye

Other information

- store at 15°-25°C (59°-77°F)
- keep tightly closed
- does not contain thimerosal
- use before expiration date marked on the bottle

Inactive ingredients

boric acid, sodium borate and sodium chloride.

PRESERVATIVE ADDED: benzalkonium chloride (0.01%)

Questions or comments?

Call: 1-888-527-4276